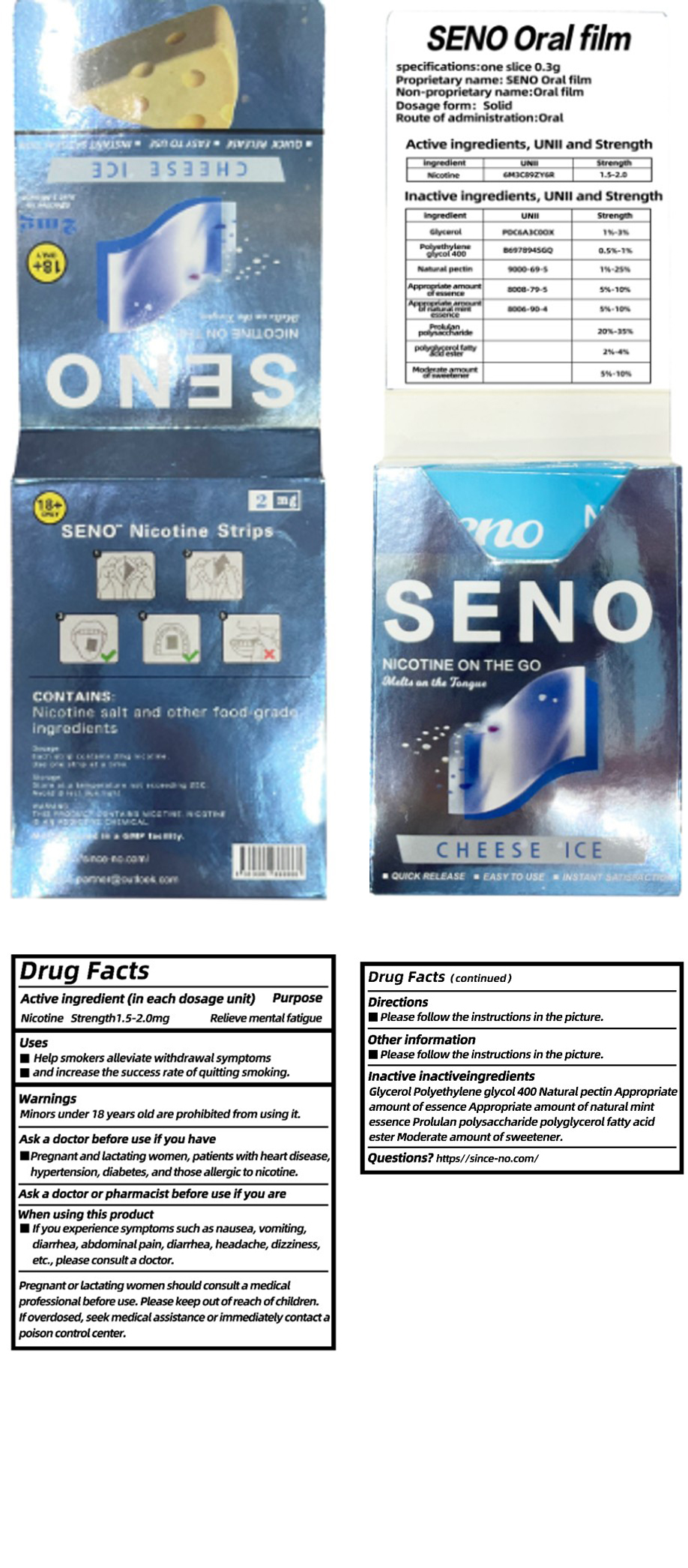 DRUG LABEL: SENO Oral film
NDC: 85806-001 | Form: FILM, SOLUBLE
Manufacturer: Xinsno Technology (Shenzhen) Co., Ltd
Category: otc | Type: HUMAN OTC DRUG LABEL
Date: 20250612

ACTIVE INGREDIENTS: NICOTINE 1.5 mg/0.3 g
INACTIVE INGREDIENTS: POLYETHYLENE GLYCOL 400; PEPPERMINT OIL; POLYGLYCEROL POLYRICINOLEIC ACID; SPEARMINT OIL; PECTIN; REBAUDIOSIDE A; GLYCERIN; XANTHAN GUM

85806-001 SENO Oral film

ACTIVE INGREDIENT

Nicotine 1.5%

PURPOSE

Relieve mental fatigue

KEEP OUT OF REACH OF CHILDREN SECTION

INDICATIONS AND USAGE

Help smokers alleviate withdrawal symptoms

and increase the success rate ofquitting smoking

WARNINGS

Minors under 18 years old are prohibited from using it.

DO NOT USE

Pregnantand lactating women, patients with heart disease,hypertension, diabetes, and those allergic to nicotine.

STOP USE

if you experience symptoms such as nausea, vomiting,diarhea,abdominalpain, diarhea, headache, dizzinessetc,please consult a doctor.

WHEN USING

Pregnantorlactating women should consutt a medical professional before use, Please keep outofreach ofchildren.lfoverdosed, seekmedical assistance orimmediately contact a poison control center.

DOSAGE AND ADMINISTRATION

Please follow the instructions in the picture

INACTIVE INGREDIENT

Glycerol
Polyethylene glycol 400
Natural pectin
Appropriate amount of essence
Appropriate amount of natural mint essence
Prolulan polysaccharide
polyglycerol fatty acid ester
Moderate amount of sweetener